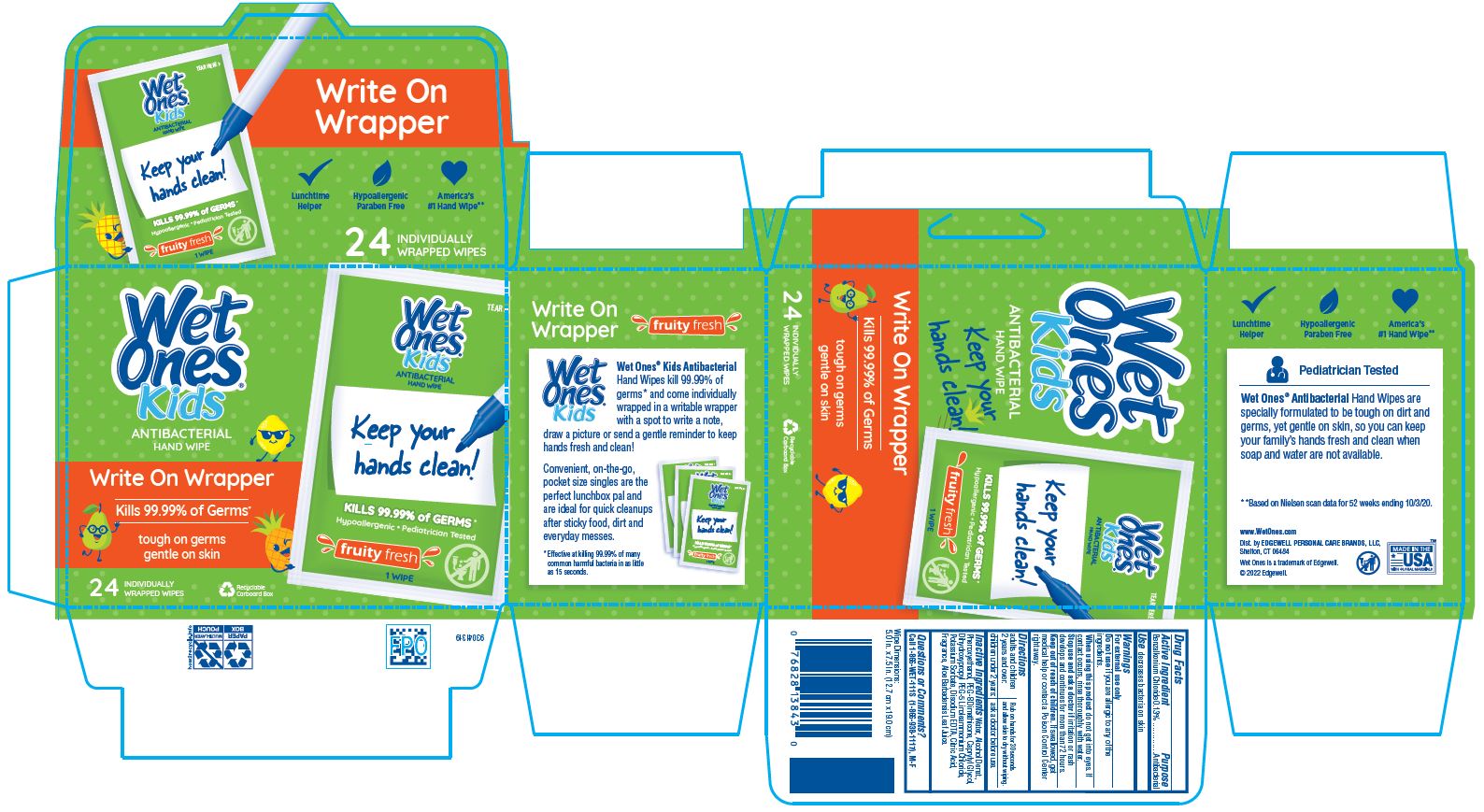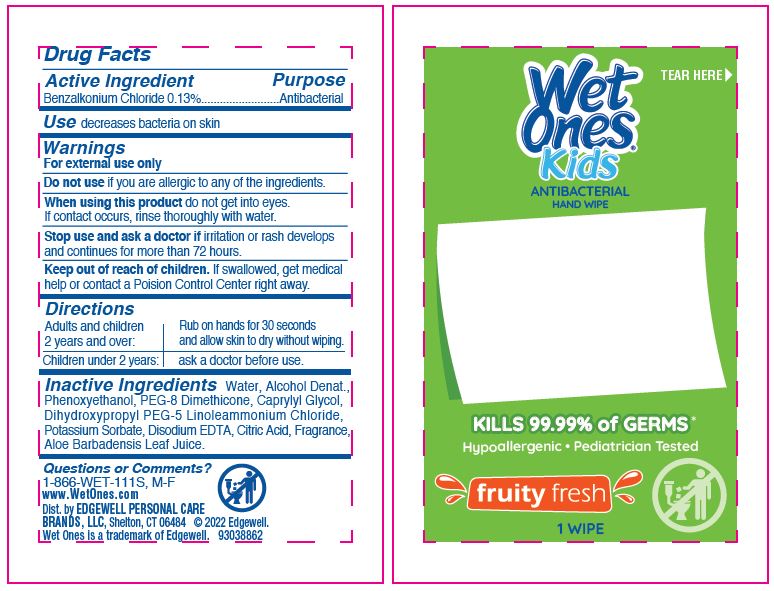 DRUG LABEL: WET ONES
NDC: 63354-926 | Form: SWAB
Manufacturer: Edgewell Personal Care Brands LLC
Category: otc | Type: HUMAN OTC DRUG LABEL
Date: 20241007

ACTIVE INGREDIENTS: BENZALKONIUM CHLORIDE 0.13 g/1 1
INACTIVE INGREDIENTS: PEG-8 DIMETHICONE; WATER; POTASSIUM SORBATE; EDETATE DISODIUM; ALCOHOL; CITRIC ACID MONOHYDRATE; CAPRYLYL GLYCOL; PHENOXYETHANOL; ALOE VERA LEAF; DIHYDROXYPROPYL PEG-5 LINOLEAMMONIUM CHLORIDE

Active Ingredient

Benzalkonium Chloride 0.13%

Purpose

Antibacterial

Use

decreases bacteria on skin

Warnings

For external use only

Do not use

if you are allergic to any of the ingredients.

When using this product

do not get into eyes. If contact occurs, rinse thoroughly with water.

Stop use and ask a doctor if

irritation or rash develops and continues for more than 72 hours.

Keep out of reach of children.

If swallowed, get medical help or contact a Poison Control Center right away.

Directions

adults and children 2 years and over: Rub on hands for 30 seconds and allow skin to dry without wiping.

children under 2 years: ask a doctor before use.

Inactive Ingredients

Water, Alcohol Denat., Phenoxyethanol, PEG-8 Dimethicone, Caprylyl Glycol, Dihydroxypropyl PEG-5 Linoleammonium Chloride, Potassium Sorbate, Disodium EDTA, Citric Acid, Fragrance, Aloe Barbadensis Leaf Juice.

Questions or Comments?

Call 1-866-WET-111S (1-866-938-1117), M-F

Principal Display Panel

TEAR HERE
Wet
Ones(R)
Kids
ANTIBACTERIAL
HAND WIPE
kills 99.99% of Germs*
Hypoallergenic Pediatrician tested
fruity fresh
1 WIPE

Wet
Ones
Kids
ANTIBACTERIAL
HAND WIPE
write On Wrapper
kills 99.99% of Germs
tough on germs
gentle on skin
24 INDIVIDUALLY
WRAPPED WIPE
Recyclable
cardboard box